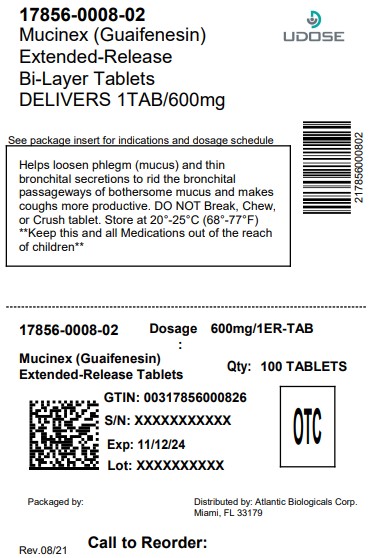 DRUG LABEL: Mucinex
NDC: 17856-0008 | Form: TABLET, EXTENDED RELEASE
Manufacturer: ATLANTIC BIOLOGICAS CORP.
Category: otc | Type: HUMAN OTC DRUG LABEL
Date: 20251204

ACTIVE INGREDIENTS: GUAIFENESIN 600 mg/1 1
INACTIVE INGREDIENTS: CARBOMER HOMOPOLYMER TYPE B (ALLYL PENTAERYTHRITOL CROSSLINKED); FD&C BLUE NO. 1; ALUMINUM OXIDE; HYPROMELLOSES; MAGNESIUM STEARATE; CELLULOSE, MICROCRYSTALLINE

Mucinex®

Drug Facts

Active ingredient (in each extended-release bi-layer tablet)

Guaifenesin 600 mg

Purpose

Expectorant

Uses

helps loosen phlegm (mucus) and thin bronchial secretions to rid the bronchial passageways of bothersome mucus and make coughs more productive

Warnings

Do not use

- for children under 12 years of age

Ask a doctor before use if you have

- persistent or chronic cough such as occurs with smoking, asthma, chronic bronchitis, or emphysema
- cough accompanied by too much phlegm (mucus)

Stop use and ask a doctor if

- cough lasts more than 7 days, comes back, or occurs with fever, rash, or persistent headache. These could be signs of a serious illness.

PREGNANCY OR BREAST FEEDING

ask a health professional before use. If pregnant or breast-feeding,

KEEP OUT OF REACH OF CHILDREN

In case of overdose, get medical help or contact a Poison Control Center right away. Keep out of reach of children.

Directions

- do not crush, chew, or break tablet
- take with a full glass of water
- this product can be administered without regard for the timing of meals
- adults and children 12 years of age and over: 1 or 2 tablets every 12 hours. Do not exceed 4 tablets in 24 hours.
- children under 12 years of age: do not use

Other information

- tamper evident: do not use if carton is open or if printed seal on blister is broken or missing
- store between 20-25°C (68-77°F)

Inactive ingredients

carbomer homopolymer type B; FD&C blue #1 aluminum lake; hypromellose, USP; magnesium stearate, NF; microcrystalline cellulose, NF; sodium starch glycolate, NF

Questions?

In case of overdose, get medical help or contact a Poison Control Center right away. (1-800-222-1222)

To report SUSPECTED ADVERSE REACTIONS, contact the FDA at 1-800-FDA-1088 or www.fda.gov/medwatch. You may also report side effects to this phone number: 1-866-MUCINEX (1-866-682-4639)

Dist. by:

ATLANTIC BIOLOGICALS CORP.

MIAMI, FL 33179